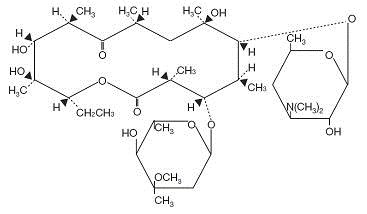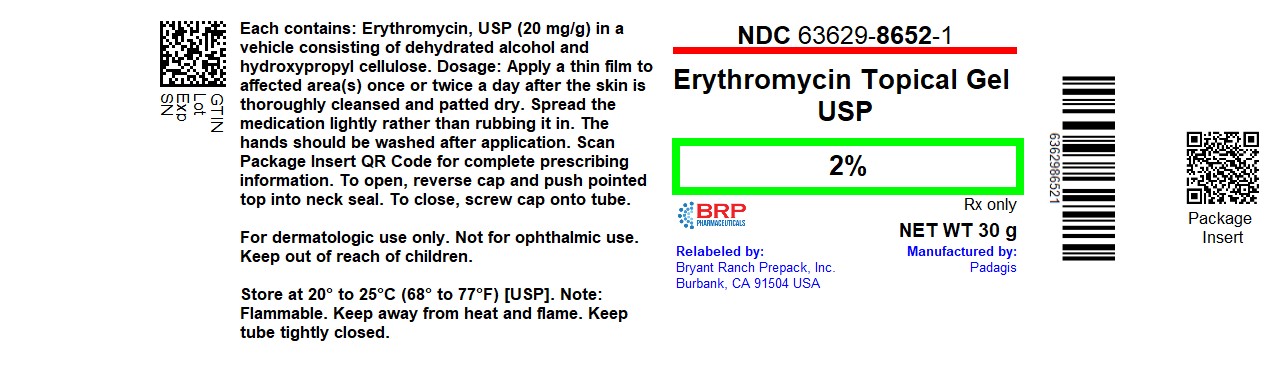 DRUG LABEL: Erythromycin
NDC: 63629-8652 | Form: GEL
Manufacturer: Bryant Ranch Prepack
Category: prescription | Type: HUMAN PRESCRIPTION DRUG LABEL
Date: 20251020

ACTIVE INGREDIENTS: ERYTHROMYCIN 20 mg/1 g
INACTIVE INGREDIENTS: ALCOHOL; HYDROXYPROPYL CELLULOSE, UNSPECIFIED

Erythromycin Topical Gel USP, 2%

For Dermatologic Use Only – Not for Ophthalmic Use

Rx Only

DESCRIPTION

Erythromycin Topical Gel USP, 2% contains erythromycin (3R*, 4S*, 5S*, 6R*, 7R*, 9R*, 11R*, 12R*, 13S*, 14R*)-4-[(2,6-Dideoxy-3-C-methyl-3-O-methyl-α-L-ribo-hexopyranosyl)oxy]-14-ethyl-7, 12, 13-trihydroxy-3, 5, 7, 9, 11, 13-hexamethyl-6-[[3, 4, 6,-trideoxy-3-(dimethylamino)-β-D-xylo-hexopyranosyl]oxy]oxacyclotetradecane-2,10-dione), for topical dermatological use. Erythromycin is a macrolide antibiotic produced from a strain of Saccaropolyspora erythraea (formerly Streptomyces erythreus). It is a base and readily forms salts with acids.

Chemically, erythromycin is C37H67NO13. It has the following structural formula:

Erythromycin has a molecular weight of 733.94. It is a white or slightly yellow, odorless or practically odorless, bitter crystalline powder. Erythromycin is very soluble in very polar organic solvents such as alcohols, acetone, chloroform, acetonitrile and ethyl acetate. It is moderately soluble in less polar solvents such as ether, dichloroethylene and amyl acetate. It is slightly soluble in nonpolar solvents such as hexane. It is very poorly soluble in water.

Each gram of Erythromycin Topical Gel USP, 2% contains 20 mg of erythromycin USP in a vehicle consisting of dehydrated alcohol and hydroxypropyl cellulose.

CLINICAL PHARMACOLOGY

The exact mechanism by which erythromycin reduces lesions of acne vulgaris is not fully known; however, the effect appears to be due in part to the antibacterial activity of the drug.

MICROBIOLOGY

Erythromycin acts by inhibition of protein synthesis in susceptible organisms by reversibly binding to 50S ribosomal subunits, thereby inhibiting translocation of aminoacyl transfer-RNA and inhibiting polypeptide synthesis. Antagonism has been demonstrated in vitro between erythromycin, lincomycin, chloramphenicol, and clindamycin.

INDICATIONS AND USAGE

Erythromycin Topical Gel USP, 2% is indicated for the topical treatment of acne vulgaris.

CONTRAINDICATIONS

Erythromycin Topical Gel USP, 2% is contraindicated in those individuals who have shown hypersensitivity to any of its components.

WARNINGS

Pseudomembranous colitis has been reported with nearly all antibacterial agents, including erythromycin, and may range in severity from mild to life-threatening. Therefore, it is important to consider this diagnosis in patients who present with diarrhea subsequent to the administration of antibacterial agents.

Treatment with antibacterial agents alters the normal flora of the colon and may permit overgrowth of clostridia. Studies indicate that a toxin produced by Clostridium difficile is one primary cause of “antibiotic-associated colitis”. After the diagnosis of pseudomembranous colitis has been established, therapeutic measures should be initiated. Mild cases of pseudomembranous colitis usually respond to drug discontinuation alone. In moderate to severe cases, consideration should be given to management with fluids and electrolytes, protein supplementation and treatment with an antibacterial drug clinically effective against C. difficile colitis.

PRECAUTIONS

General -

For topical use only; not for ophthalmic use. Concomitant topical acne therapy should be used with caution because a possible cumulative irritancy effect may occur, especially with the use of peeling, desquamating or abrasive agents.

Avoid contact with eyes and all mucous membranes.

The use of antibiotic agents may be associated with the overgrowth of antibiotic-resistant organisms. If this occurs, discontinue use and take appropriate measures.

Information For Patients -

Patients using Erythromycin Topical Gel USP, 2% should receive the following information and instructions:

1. This medication is to be used as directed by the physician. It is for external use only. Avoid contact with the eyes, nose, mouth, and all mucous membranes.
2. This medication should not be used for any disorder other than that for which it was prescribed.
3. Patients should not use any other topical acne medication unless otherwise directed by their physician.
4. Patients should report to their physician any signs of local adverse reactions.

Carcinogenesis, Mutagenesis, Impairment of Fertility -

No animal studies have been performed to evaluate carcinogenic and mutagenic potential, or effects on fertility of topical erythromycin. However, long-term (2-year) oral studies in rats with erythromycin ethylsuccinate and erythromycin base did not provide evidence of tumorigenicity. There was no apparent effect on male or female fertility in rats fed erythromycin (base) at levels up to 0.25% of diet.

Pregnancy:

Teratogenic Effects: Pregnancy Category B - There was no evidence of teratogenicity or any other adverse effect on reproduction in female rats fed erythromycin base (up to 0.25% of diet) prior to and during mating, during gestation and through weaning of two successive litters. There are, however, no adequate and well-controlled studies in pregnant women. Because animal reproduction studies are not always predictive of human response, this drug should be used in pregnancy only if clearly needed. Erythromycin has been reported to cross the placental barrier in humans, but fetal plasma levels are generally low.

Nursing Women -

It is not known whether erythromycin is excreted in human milk after topical application. However, erythromycin is excreted in human milk following oral and parenteral erythromycin administration. Therefore, caution should be exercised when erythromycin is administered to a nursing woman.

Pediatric Use -

Safety and effectiveness in pediatric patients have not been established.

KEEP OUT OF REACH OF CHILDREN.

ADVERSE REACTIONS

In controlled clinical trials, the incidence of burning associated with erythromycin topical gel USP, 2% was approximately 25%. The following additional local adverse reactions have been reported occasionally: peeling, dryness, itching, erythema, and oiliness. Irritation of the eyes and tenderness of the skin have also been reported with the topical use of erythromycin. A generalized urticarial reaction, possibly related to the use of erythromycin, which required systemic steroid therapy has been reported.

DOSAGE AND ADMINISTRATION

Erythromycin Topical Gel USP, 2% should be applied sparingly as a thin film to affected area(s) once or twice a day after the skin is thoroughly cleansed and patted dry. If there has been no improvement after 6 to 8 weeks, or if the condition becomes worse, treatment should be discontinued, and the physician should be reconsulted. Spread the medication lightly rather than rubbing it in. There are no data directly comparing the safety and efficacy of b.i.d. versus q.d. dosing.

HOW SUPPLIED

Erythromycin Topical Gel USP, 2% is available as follows:

30 g sealed metal tube (NDC 63629-8652-1)

Repackaged/Relabeled by:
Bryant Ranch Prepack, Inc. Burbank, CA 91504

STORAGE

Note - FLAMMABLE. Keep away from heat and flame. Store and dispense in original container. Keep tube tightly closed. Store at 20-25°C (68-77°F) [see USP Controlled Room Temperature].

Made in Israel

Manufactured by Perrigo
Yeruham, Israel

Distributed By
Perrigo®
Allegan, MI 49010
www.perrigo.com

Rev 01-19

6J400 RC J6

PACKAGE LABEL

Erythromycin 2% Gel, #30